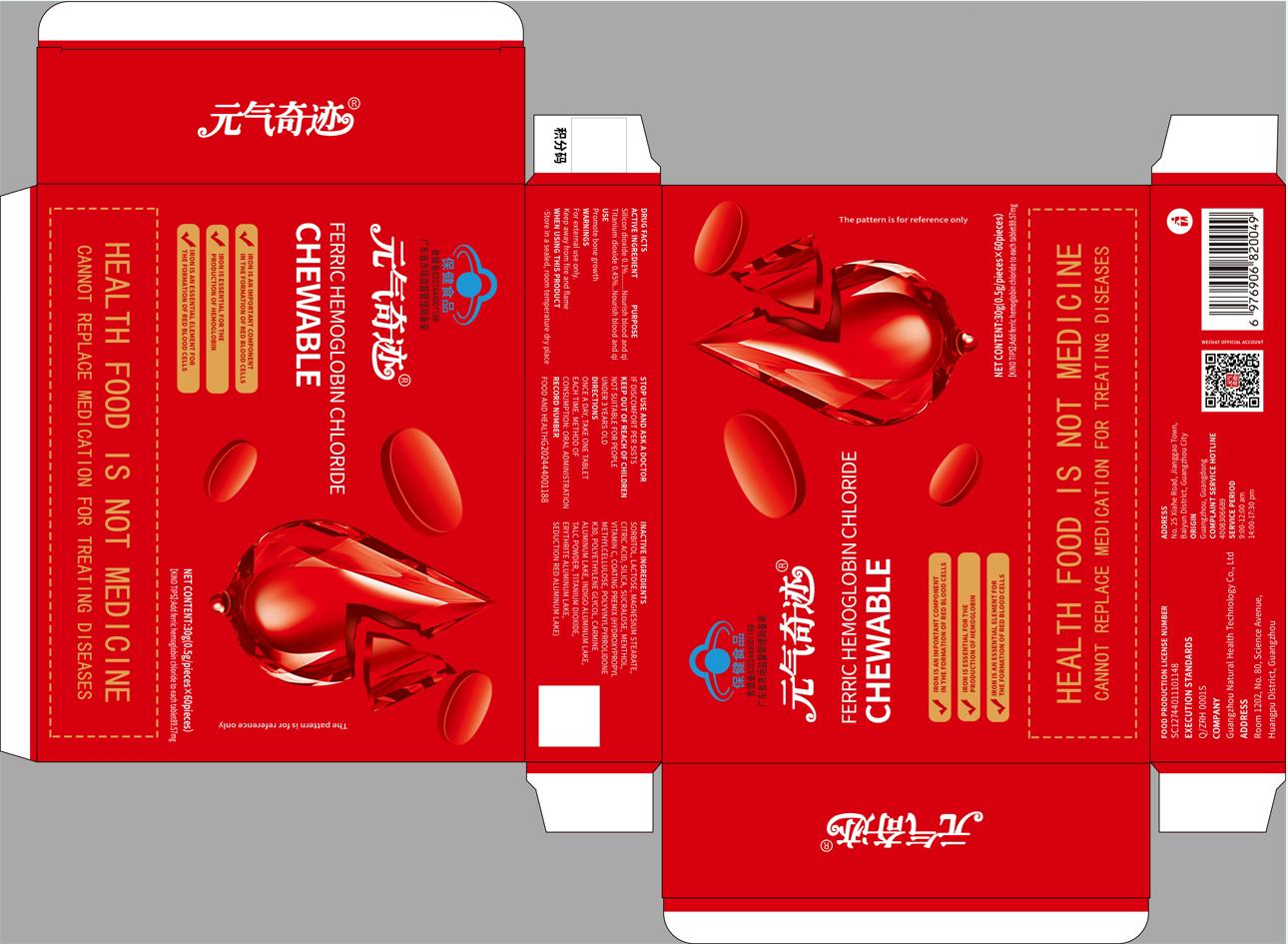 DRUG LABEL: FERRIC HEMOGLOBIN CHLORIDE
NDC: 84634-004 | Form: TABLET
Manufacturer: Guangzhou Natural Health Technology Co., Ltd
Category: otc | Type: HUMAN OTC DRUG LABEL
Date: 20240815

ACTIVE INGREDIENTS: SILICON DIOXIDE 0.1 g/100 g; TITANIUM DIOXIDE 0.45 g/100 g
INACTIVE INGREDIENTS: MAGNESIUM STEARATE; POLYETHYLENE GLYCOL, UNSPECIFIED; ASCORBIC ACID; TALC; FD&C RED NO. 40 ALUMINUM LAKE; POVIDONE K30; SUCRALOSE; SORBITOL; CITRIC ACID MONOHYDRATE; LACTOSE, UNSPECIFIED FORM; MENTHOL; HYPROMELLOSES; ALUMINUM OXIDE

ACTIVE INGREDIENT

Silicon dioxide is 0.1%

Titanium dioxide 0.45%

PURPOSE

Nourish blood and qi

Nourish blood and qi

INDICATIONS AND USAGE

Promote bone growth

WARNINGS

For external use only.

Keep away from fire and flame

WHEN USING THIS PRODUCT

·Store in a sealed, room temperature dry place

STOP USE AND ASK A DOCTOR

IF DISCOMFORT PER SISTS

KEEP OUT OF REACH OF CHILDREN

NOT SUITABLE FOR PEOPLE UNDER 3 YEARS OLD

DIRECTIONS

ONCE A DAY, TAKE ONE TABLET EACH TIME. METHOD OF

CONSUMPTION: ORAL ADMINISTRATION RECORD NUMBER FO0D AND HEALTHG202444001188

INACTIVE INGREDIENT

SORBITOL, LACTOSE, MAGNESIUM STEARATE, CITRIC ACID, SILICA, SUCRALOSE, MENTHOL, VITAMIN C, COATING PREMIX (HYDROXYPROPYL METHYLCELLULOSE, POLYVINYLPYRROLIDONE K30, POLYETHYLENE GLYCOL, CARMINE ALUMINUM LAKE, INDIGO ALUMINUM LAKE, TALC POWDER, TITANIUM DIOXIDE, ERYTHRITE ALUMINUM LAKE, SEDUCTION RED ALUMINUM LAKE)